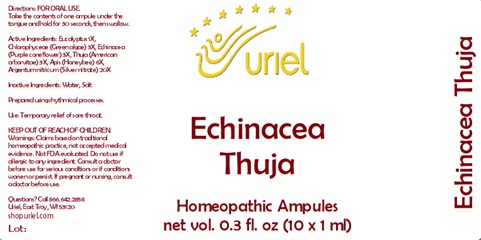 DRUG LABEL: Echinacea Thuja
NDC: 48951-4021 | Form: LIQUID
Manufacturer: Uriel Pharmacy Inc.
Category: homeopathic | Type: HUMAN OTC DRUG LABEL
Date: 20241203

ACTIVE INGREDIENTS: EUCALYPTUS GUM 1 [hp_X]/1 mL; CHLOROPHYLL 3 [hp_X]/1 mL; ECHINACEA, UNSPECIFIED 3 [hp_X]/1 mL; THUJA OCCIDENTALIS WHOLE 3 [hp_X]/1 mL; APIS MELLIFERA 6 [hp_X]/1 mL; SILVER 20 [hp_X]/1 mL
INACTIVE INGREDIENTS: WATER; SODIUM CHLORIDE

Echinacea Thuja

INDICATIONS AND USAGE

Directions: FOR ORAL USE.

DOSAGE AND ADMINISTRATION

Take the contents of one ampule under the tongue and hold for 30 seconds, then swallow.

ACTIVE INGREDIENT

Active Ingredients: Eucalyptus 1X, Chlorophyceae (Green algae) 3X, Echinacea (Purple coneflower) 3X, Thuja (American arborvitae) 3X, Apis (Honeybee) 6X, Argentum nitricum (Silver nitrate) 20X

Inactive Ingredients: Water, Salt

Prepared using rhythmical processes.

PURPOSE

Use: Temporary relief of sore throat.

KEEP OUT OF REACH OF CHILDREN.

WARNINGS

Warnings: Claims based on traditional homeopathic practice, not accepted medical evidence. Not FDA evaluated. Do not use if allergic to any ingredient. Consult a doctor before use for serious conditions or if conditions worsen or persist. If pregnant or nursing, consult a doctor before use.

QUESTIONS

Questions? Call 866.642.2858 Uriel, East Troy, WI 53120 shopuriel.com Lot: